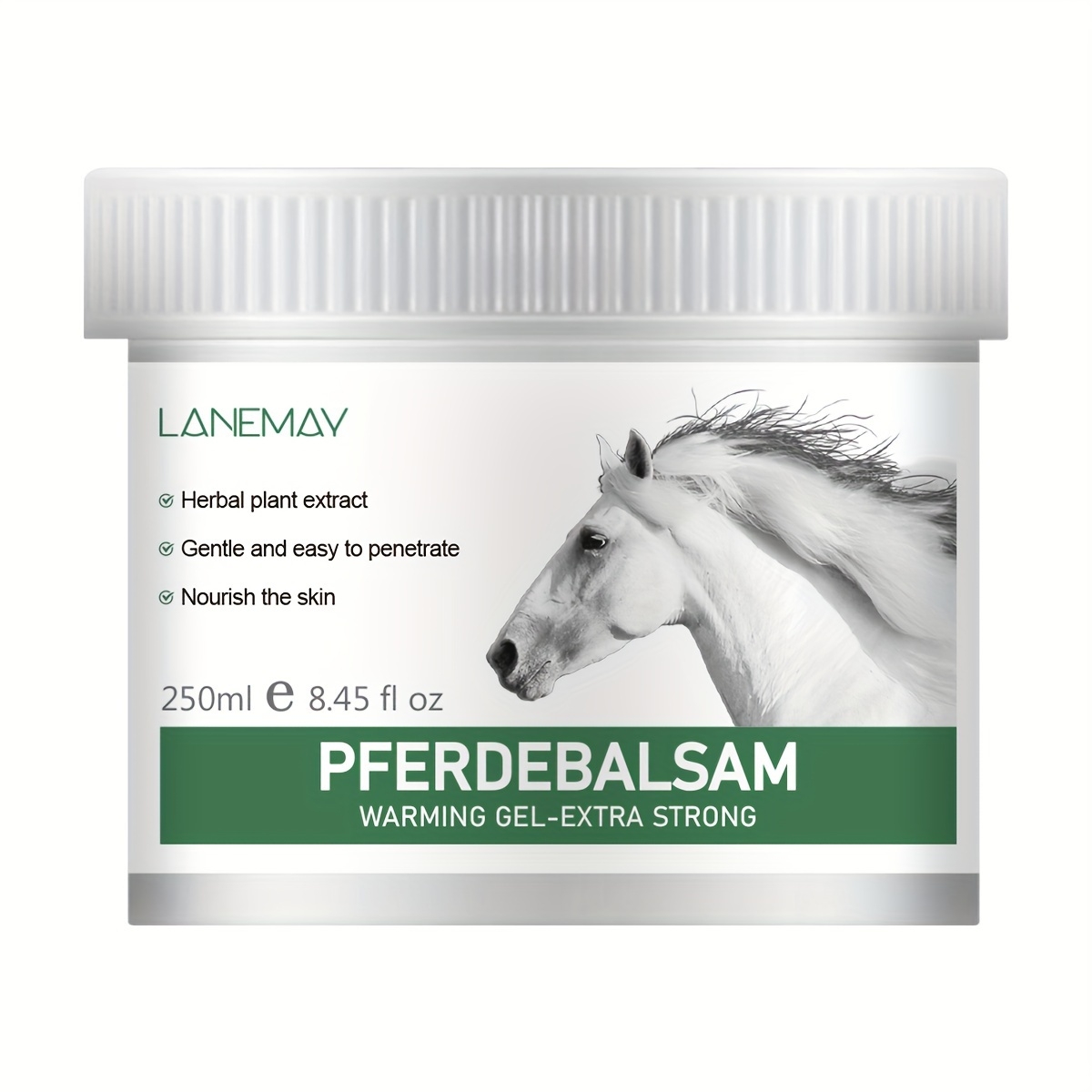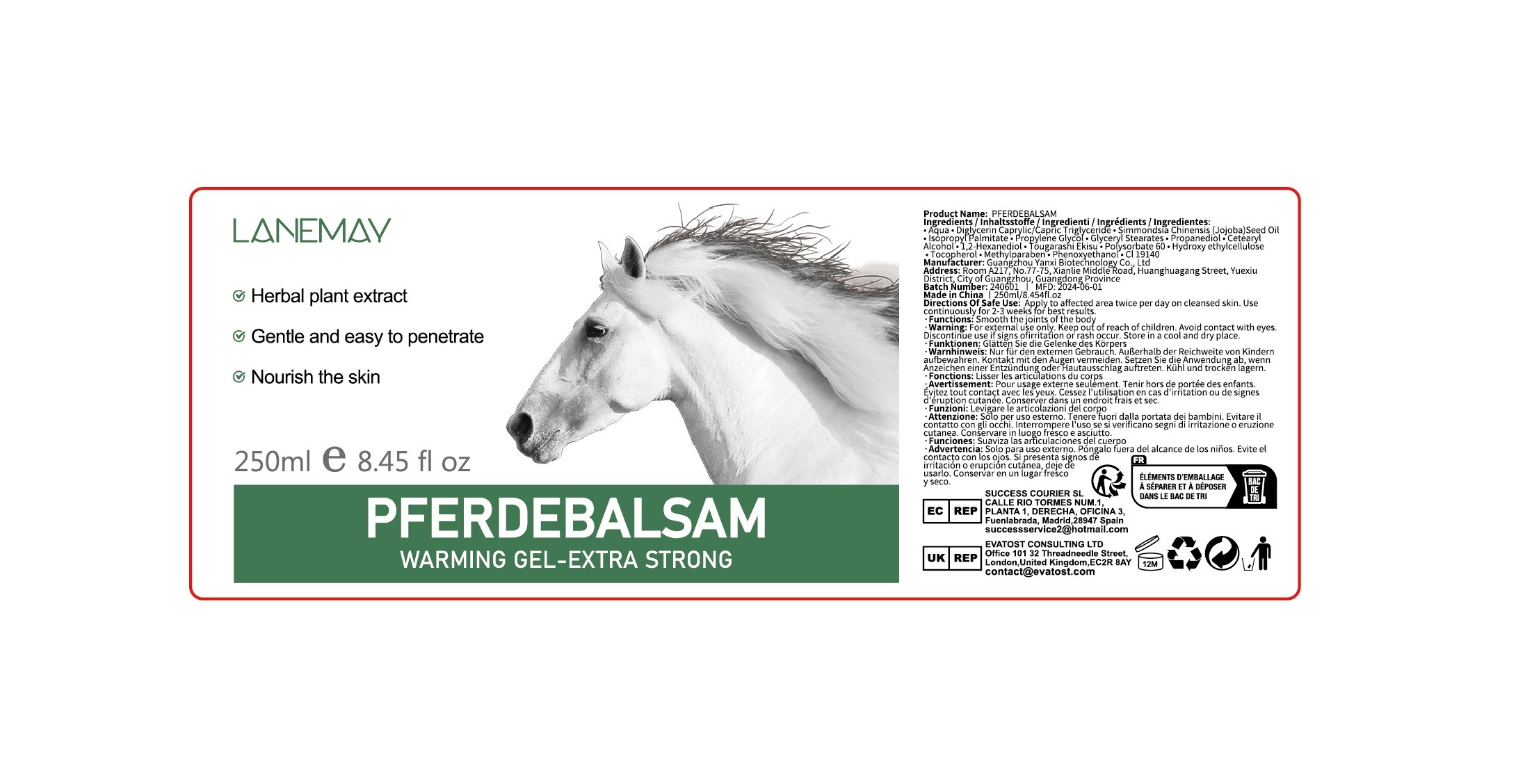 DRUG LABEL: PFERDEBALSAM
NDC: 84025-230 | Form: CREAM
Manufacturer: Guangzhou Yanxi Biotechnology Co., Ltd
Category: otc | Type: HUMAN OTC DRUG LABEL
Date: 20241023

ACTIVE INGREDIENTS: ISOPROPYL PALMITATE 12 mg/250 mL; TOCOPHEROL 10 mg/250 mL
INACTIVE INGREDIENTS: WATER

DOSAGE AND ADMINISTRATION

Apply to affected area twice per day on cleansed skin

WARNINGS

Keep out of children

INACTIVE INGREDIENT

Aqua

INDICATIONS AND USAGE

For daily skin care

Keep out of children

PURPOSE

Smooth the joints of the body